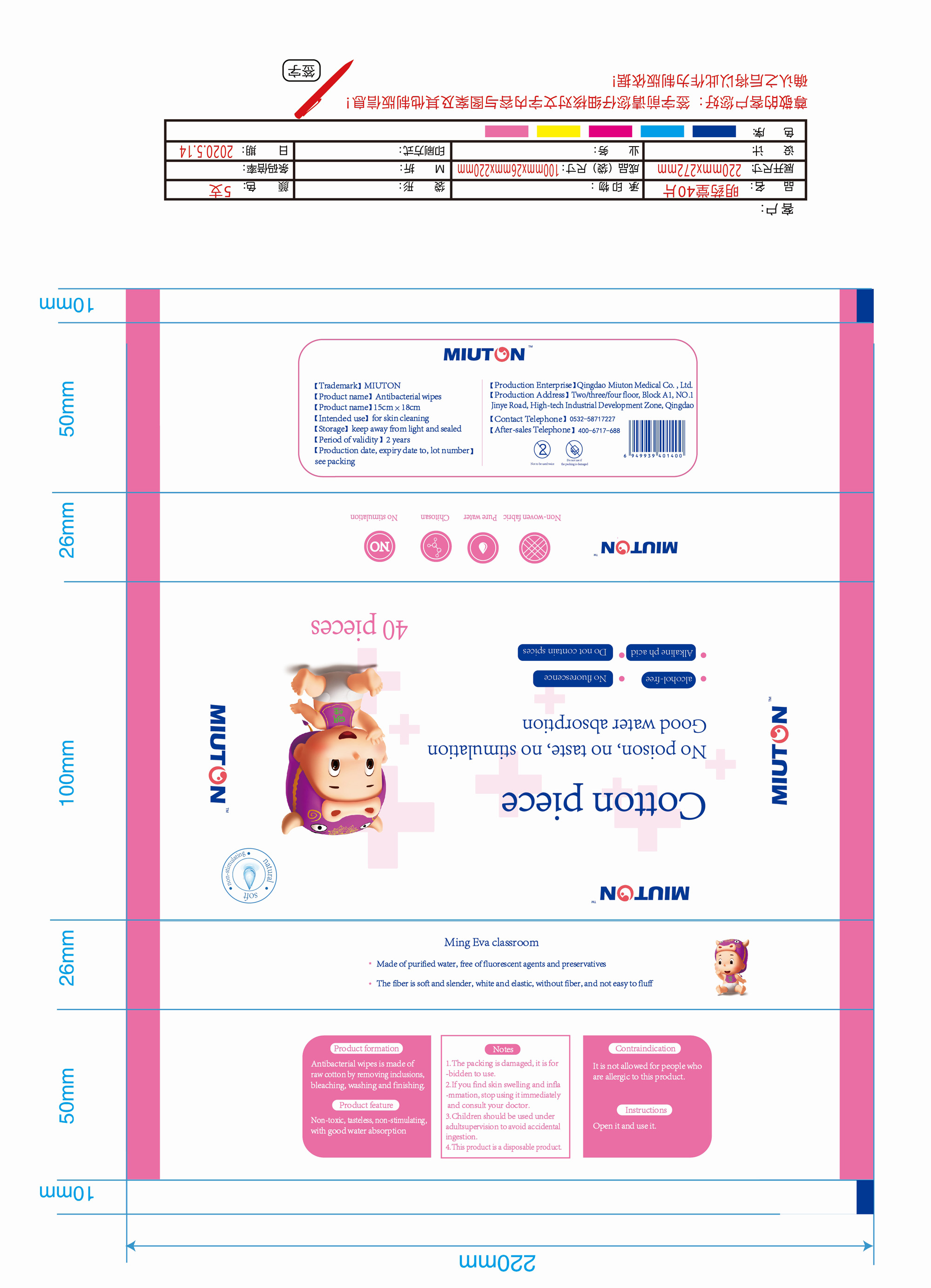 DRUG LABEL: Cotton piece
NDC: 90059-002 | Form: CLOTH
Manufacturer: Qingdao Miuton Medical Co.,LTD.
Category: otc | Type: HUMAN OTC DRUG LABEL
Date: 20200804

ACTIVE INGREDIENTS: POLIGLUSAM 0.01 g/1000 g
INACTIVE INGREDIENTS: WATER

Drug Facts

Active Ingredient(s)

Chitosan 0.01g in 1000g

Purpose

Antiseptic

Use

For skin cleaning.

Warnings

For external use only. It is not allowed for people who are allergic to this product.

STOP USE

If you find skin swelling and inflammation, stop using it immediately and consult your doctor.

KEEP OUT OF REACH OF CHILDREN

Children should be used under adult supervision to avoid accidental ingestion.

Directions

Open it and use it.

Other information

Keep away from light and sealed.

Inactive ingredients

Water, Non-woven fabric